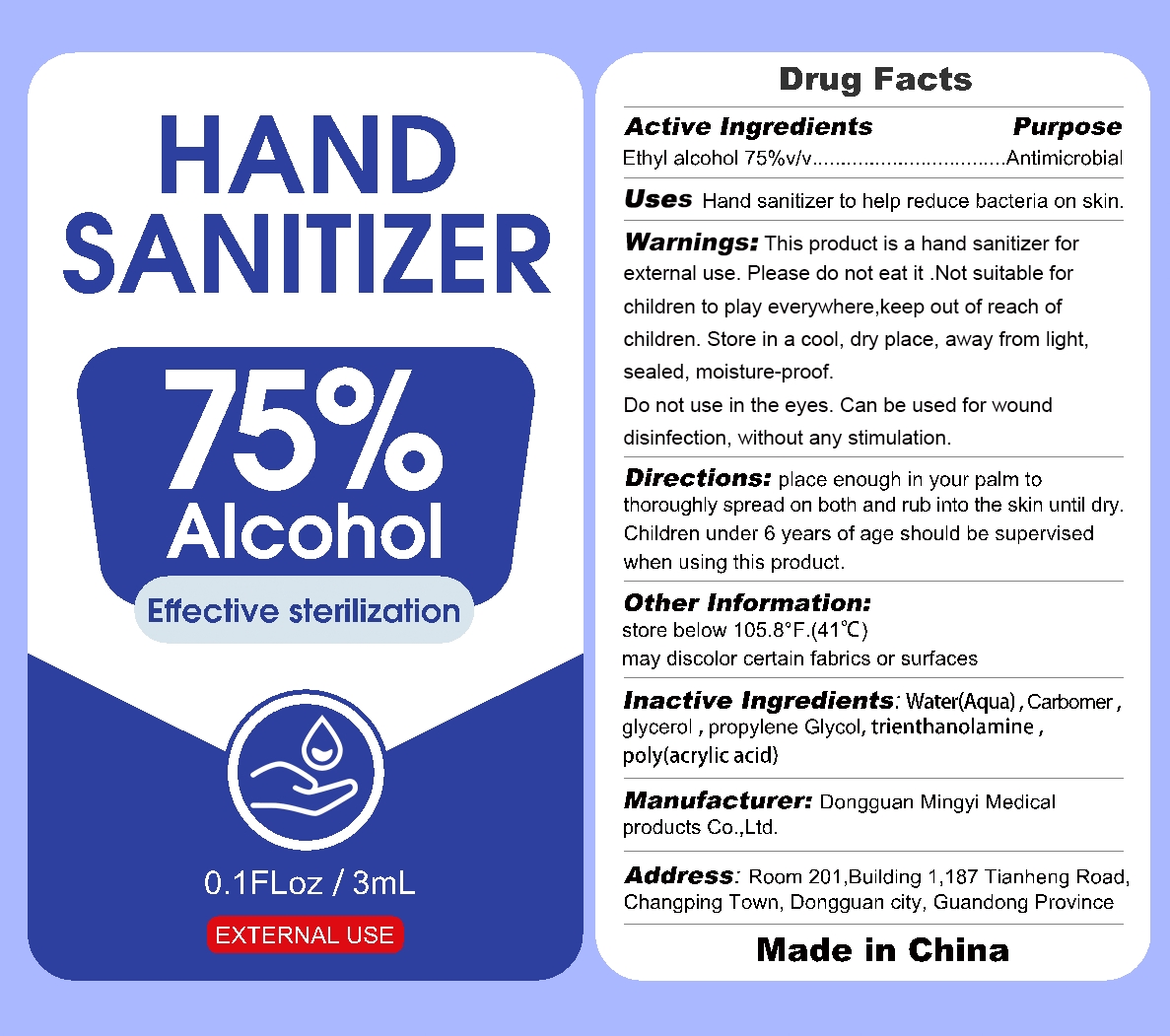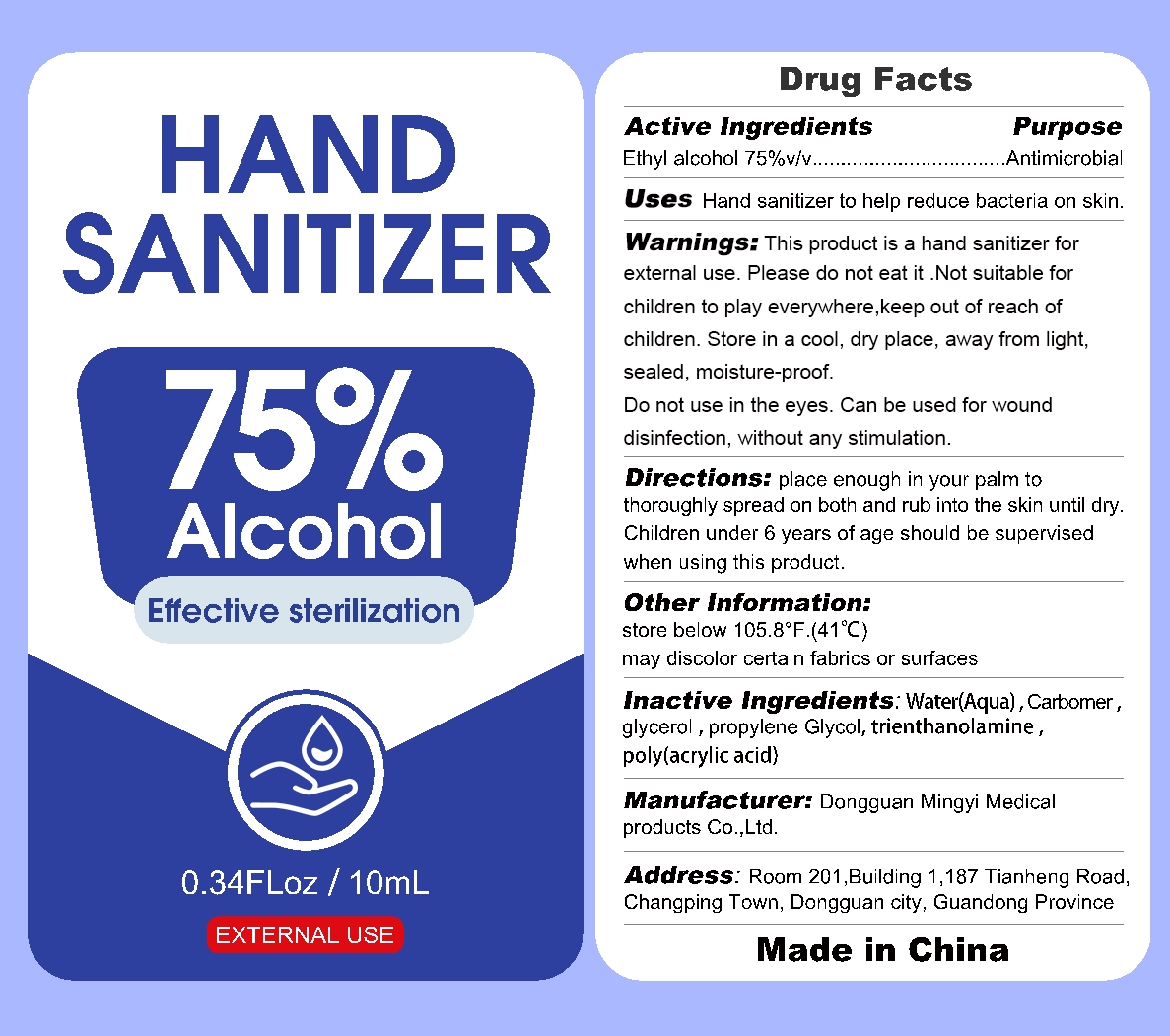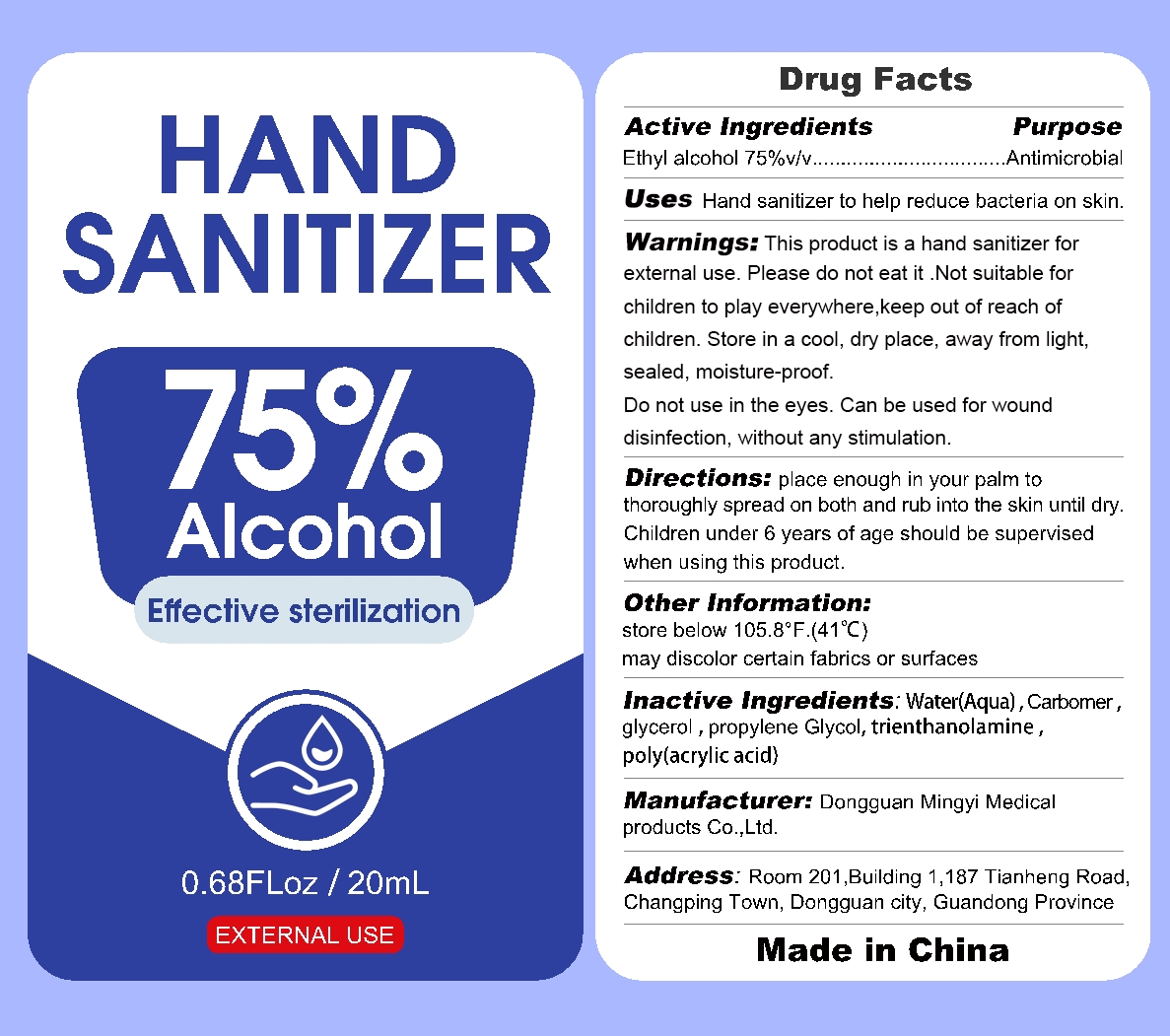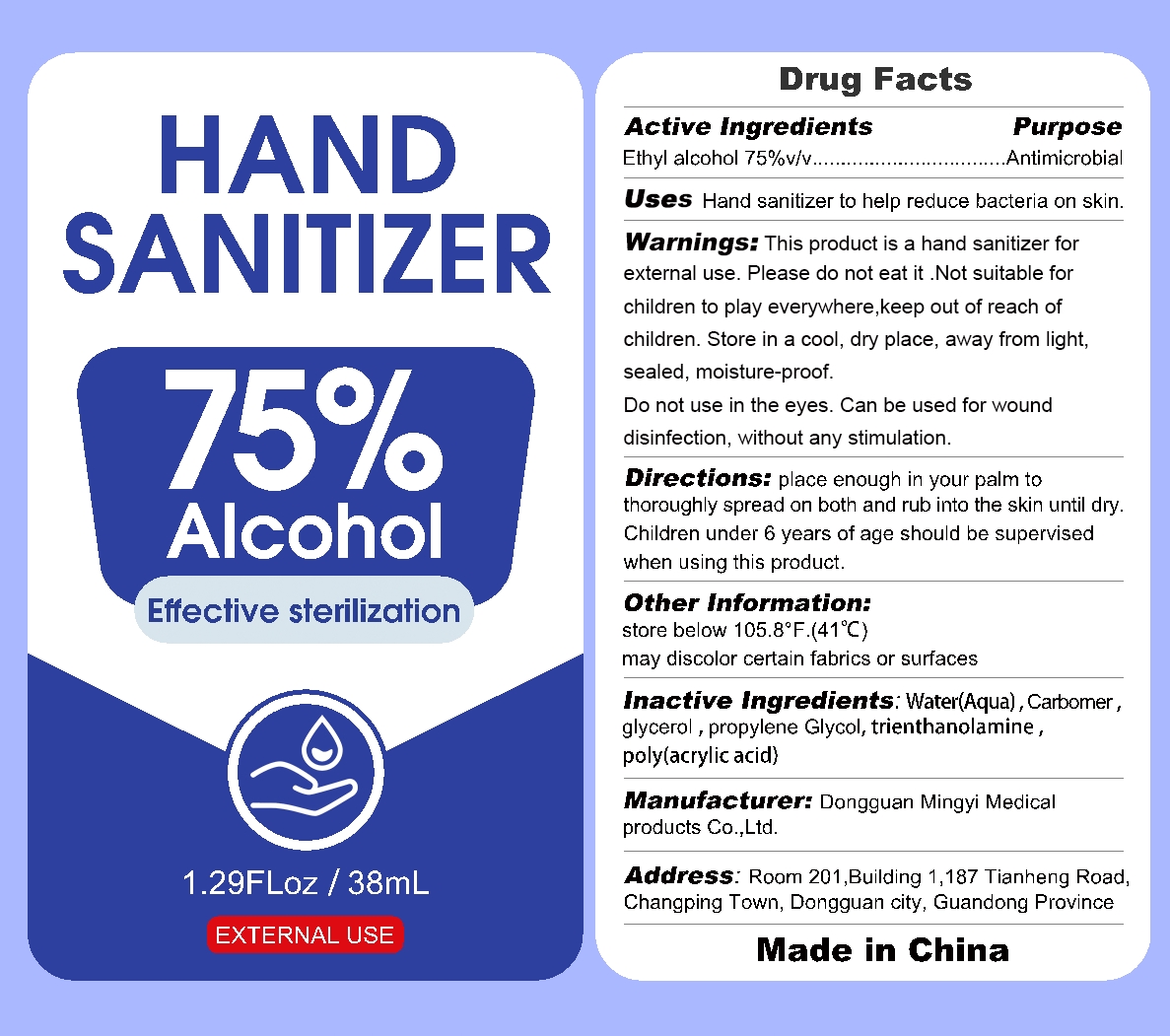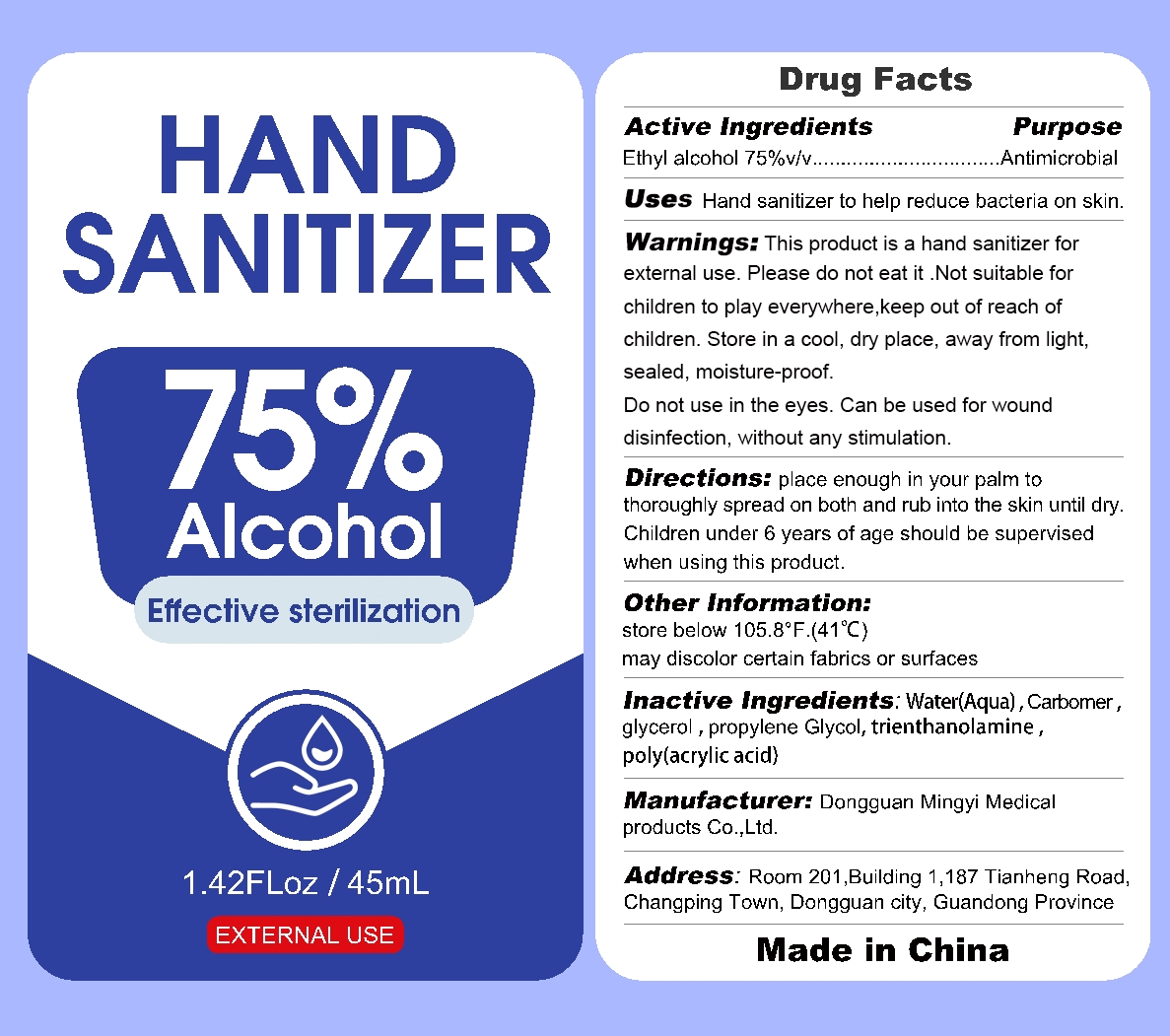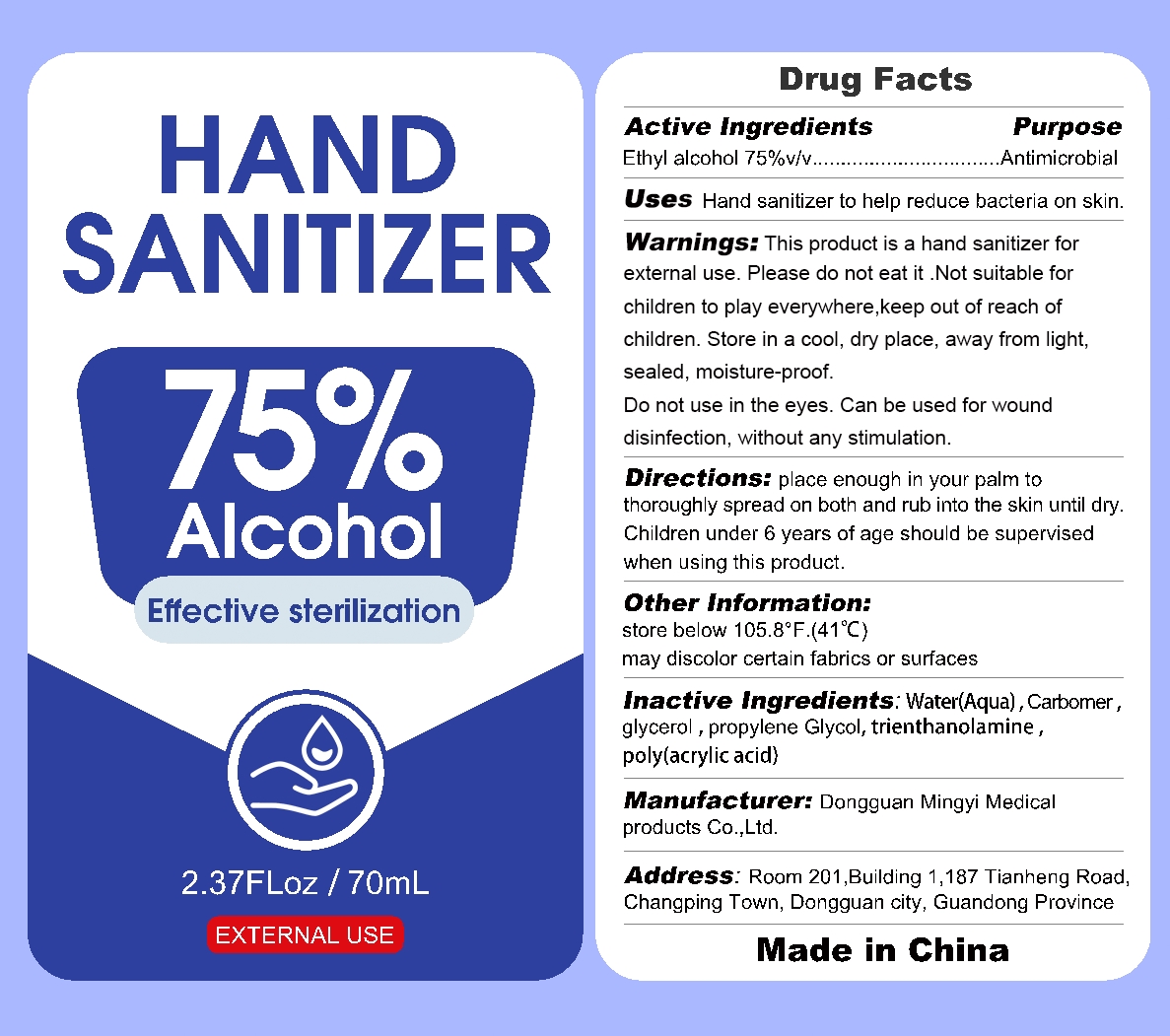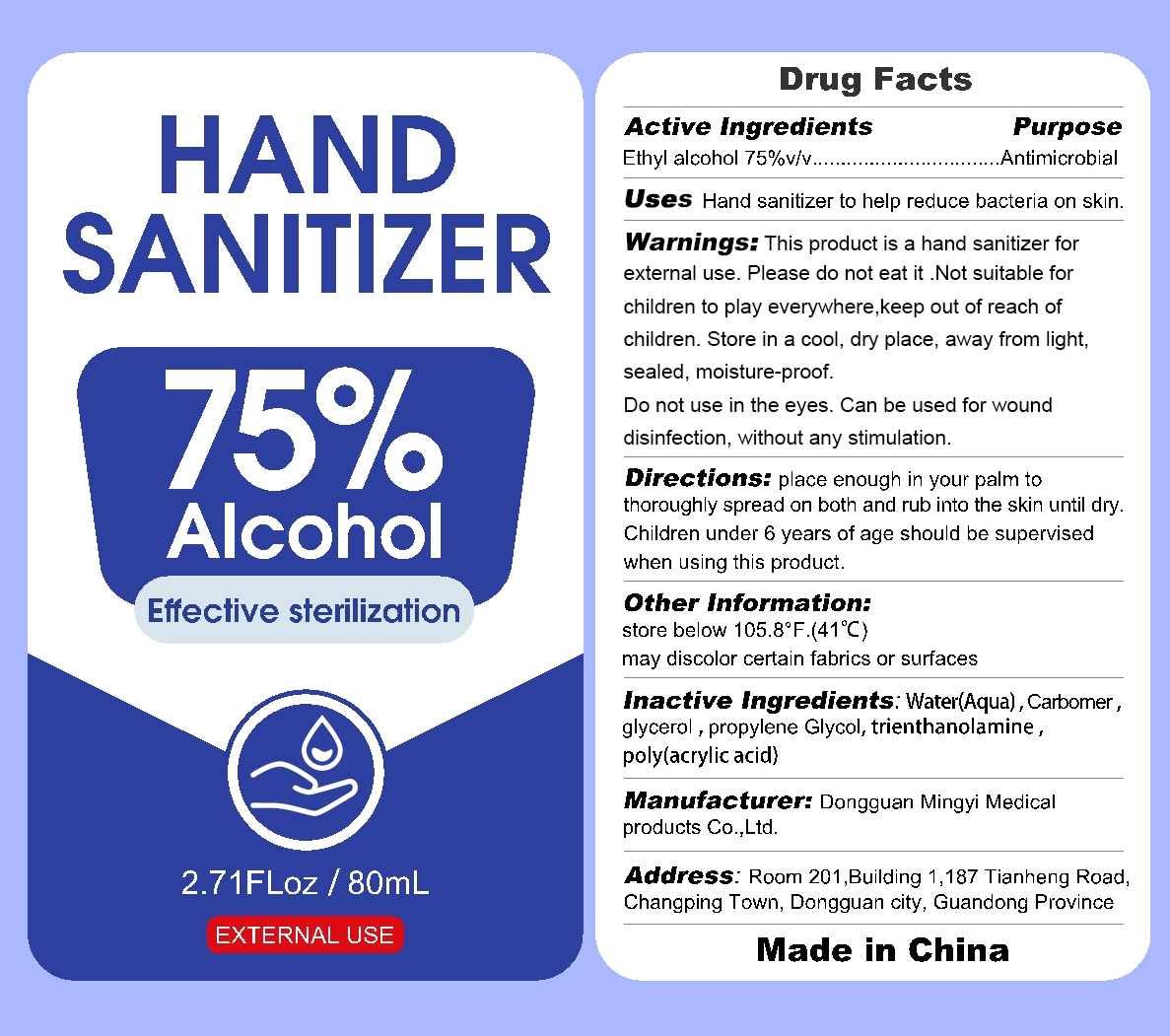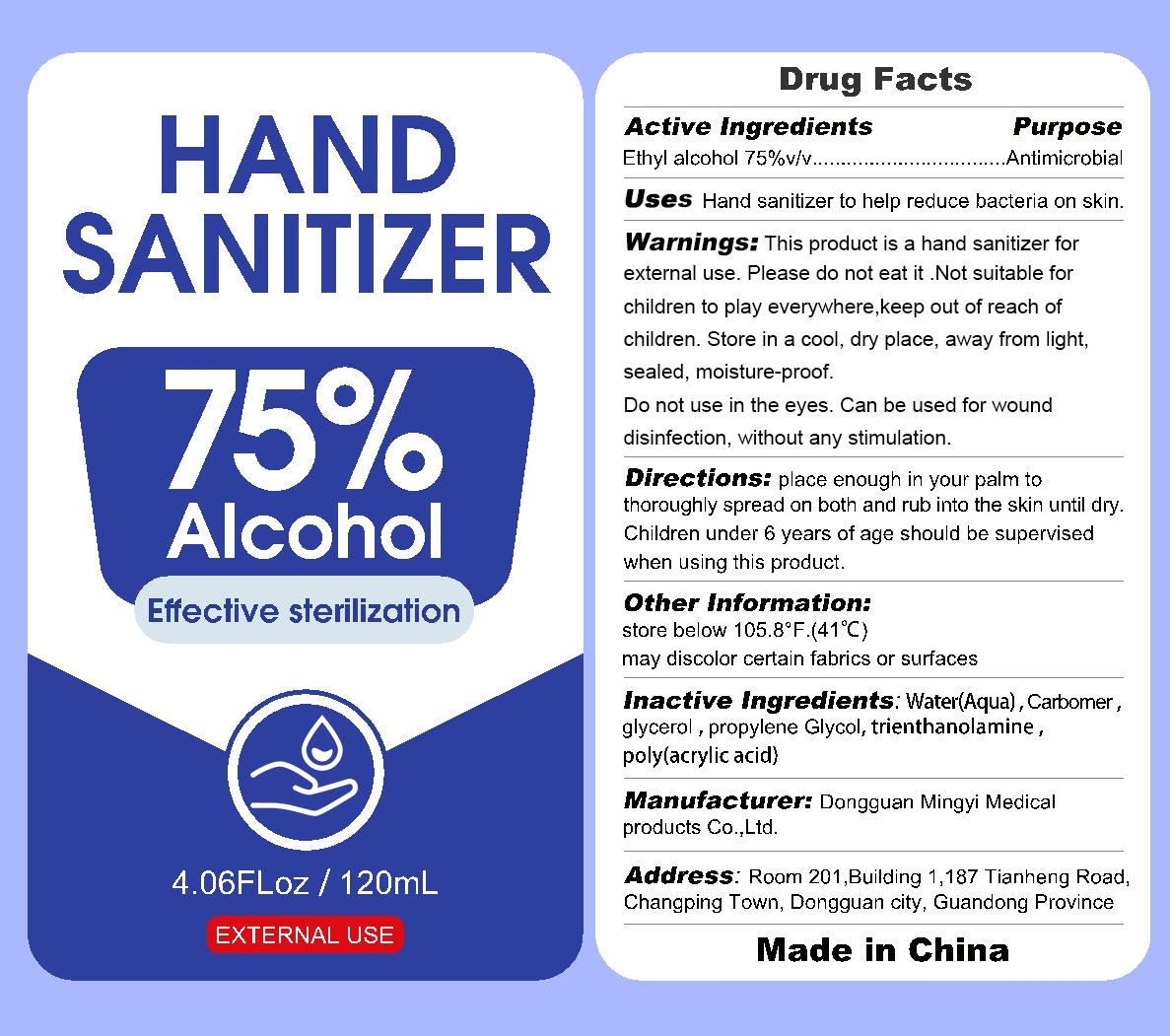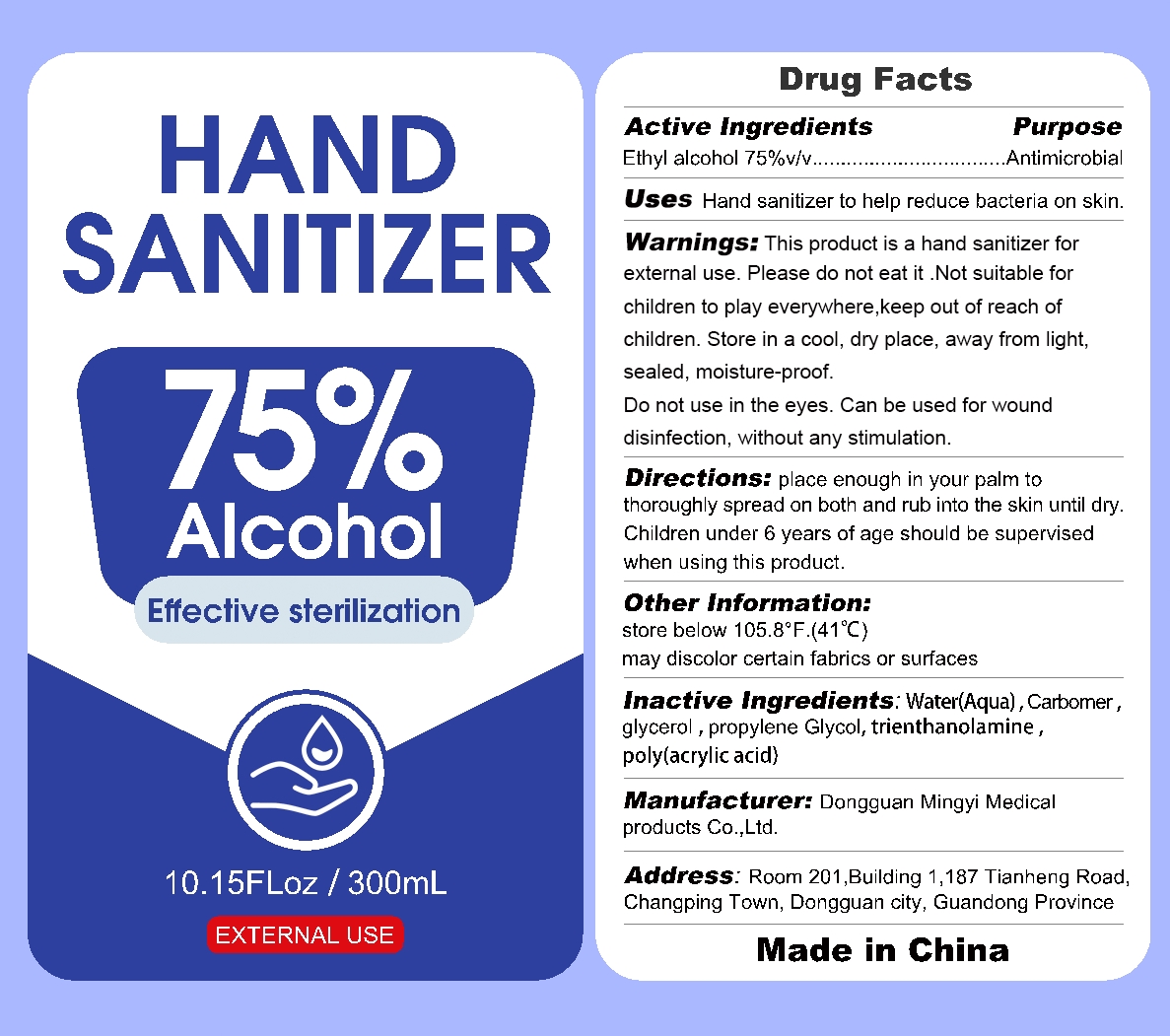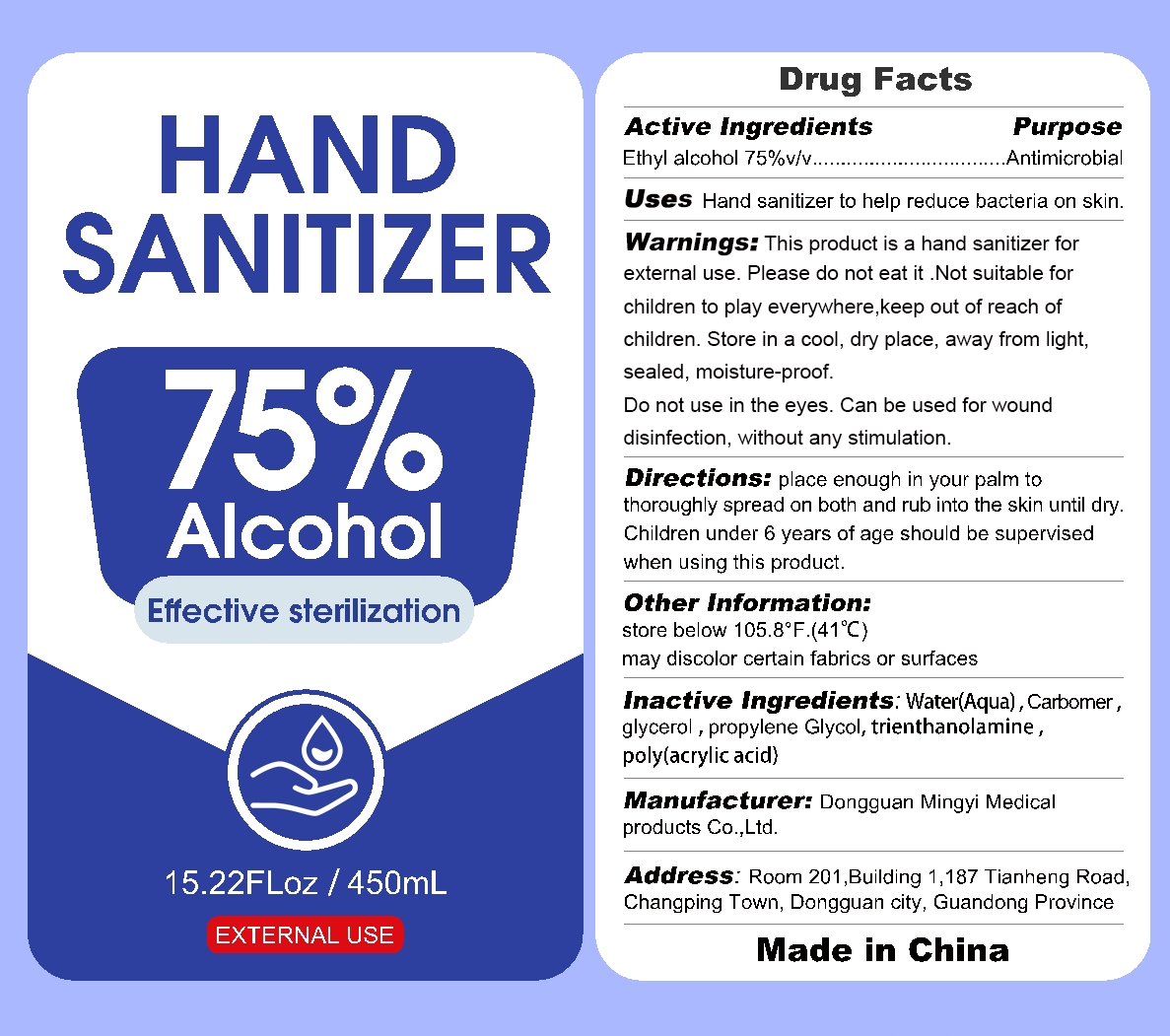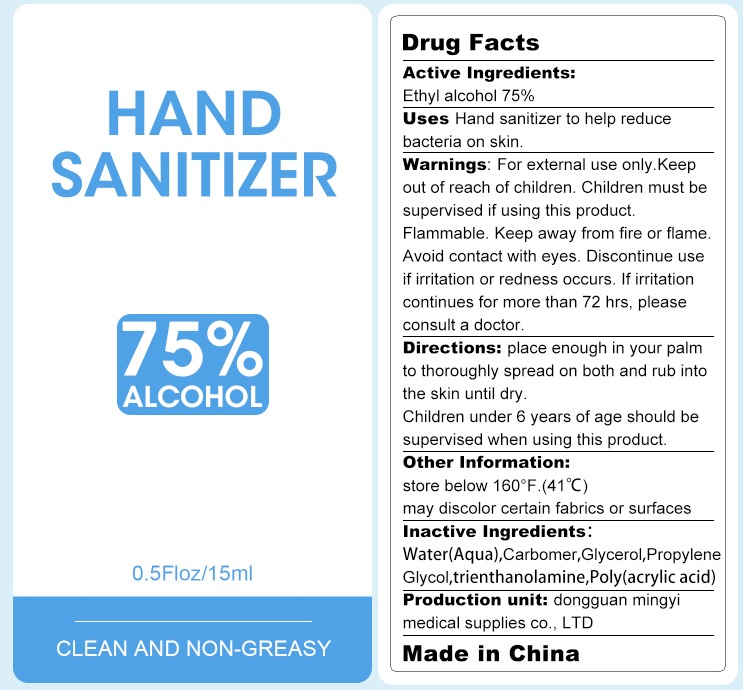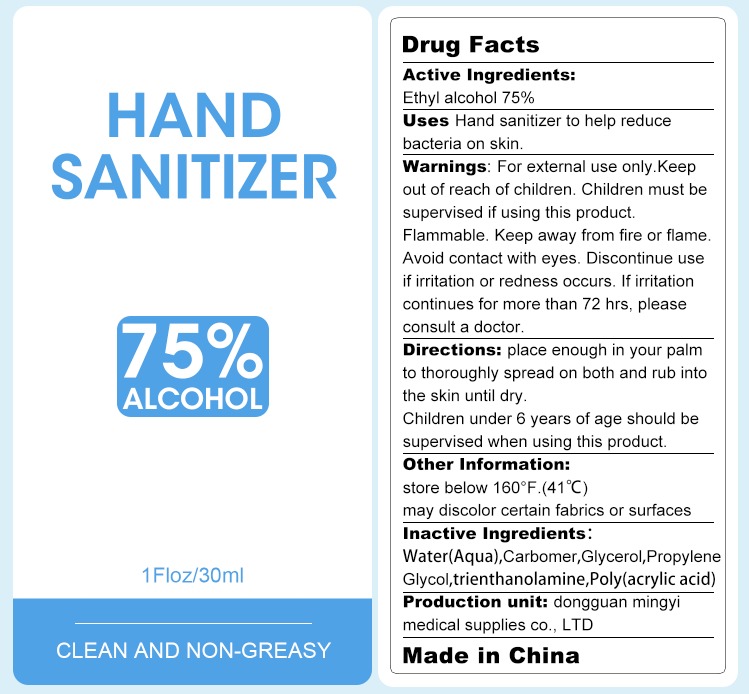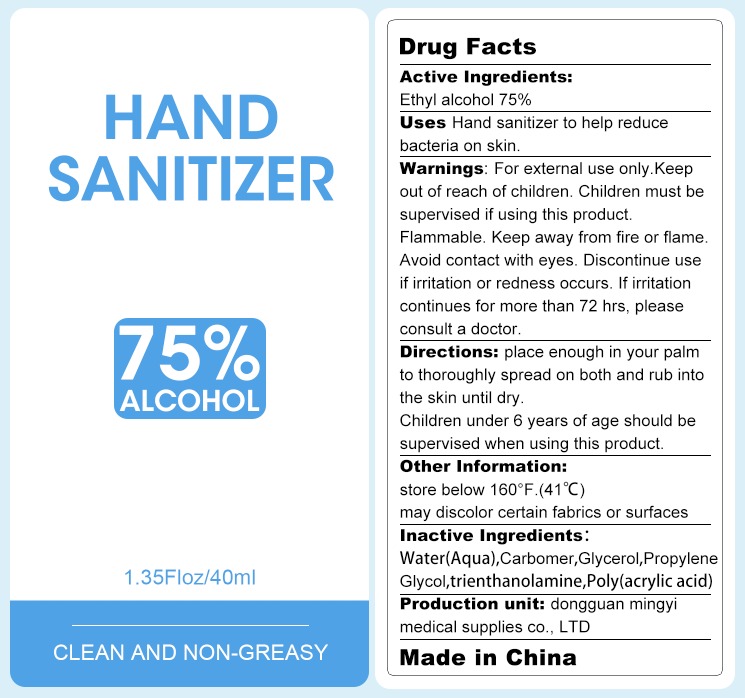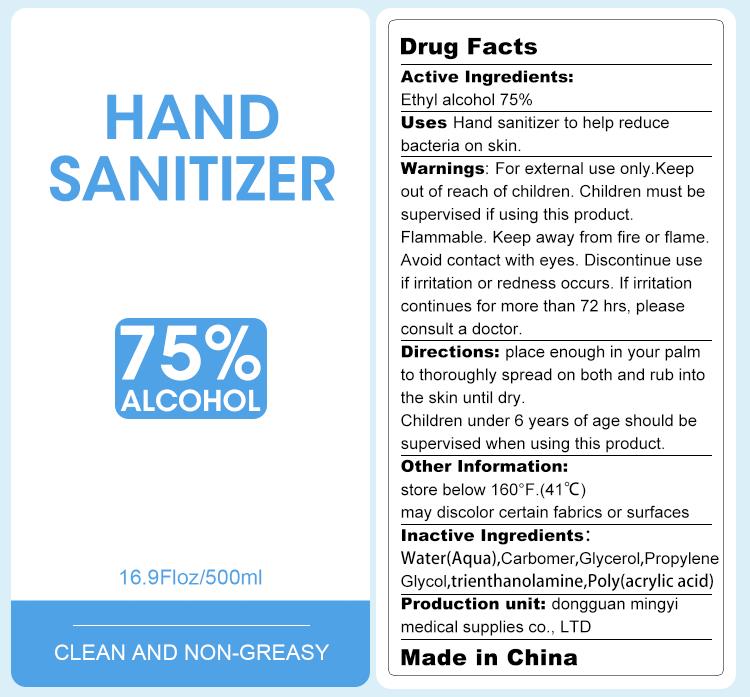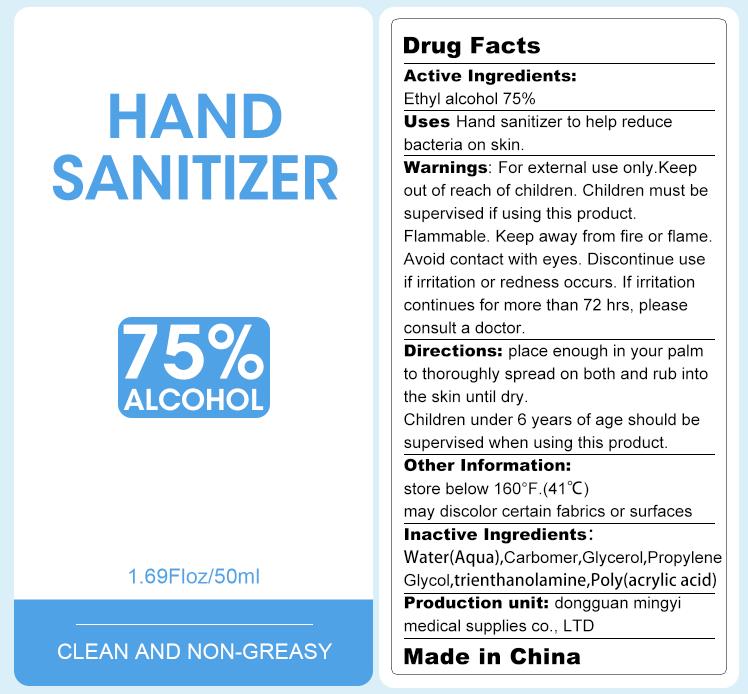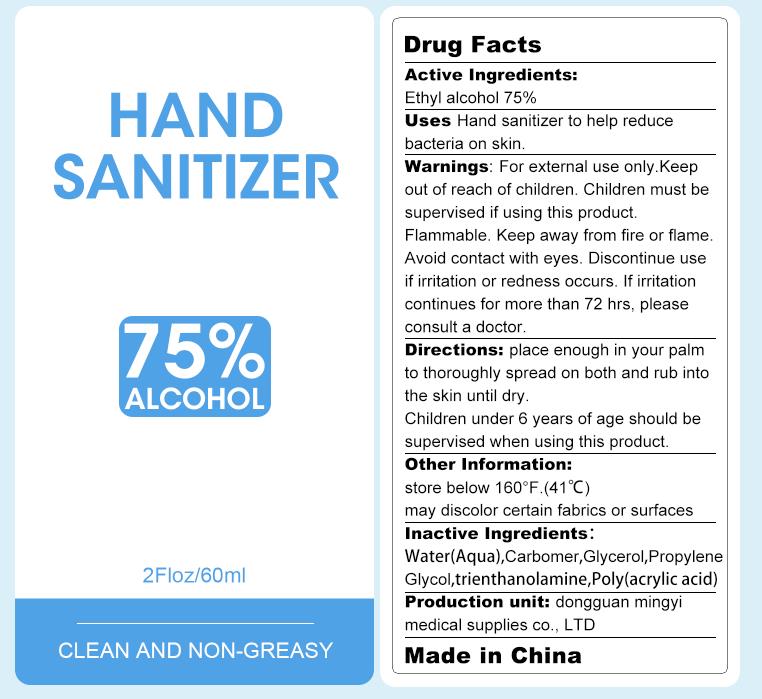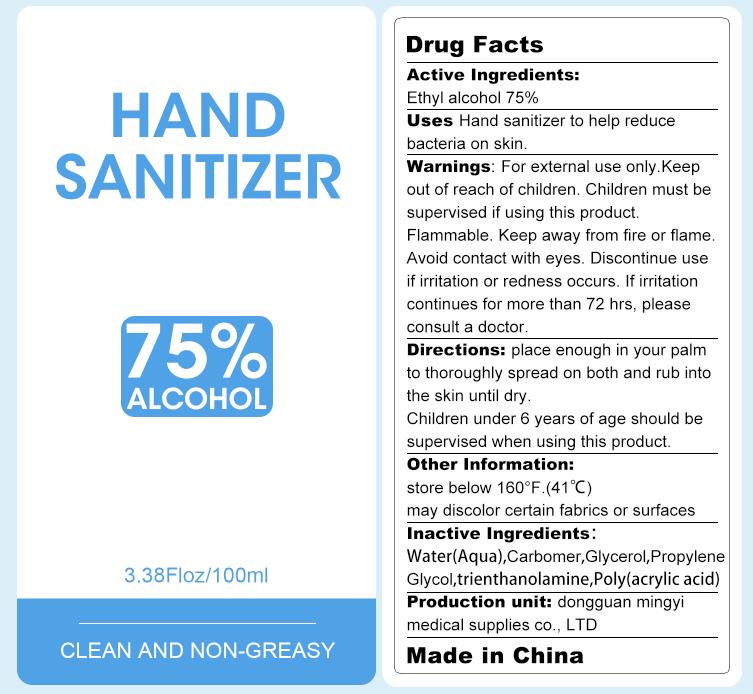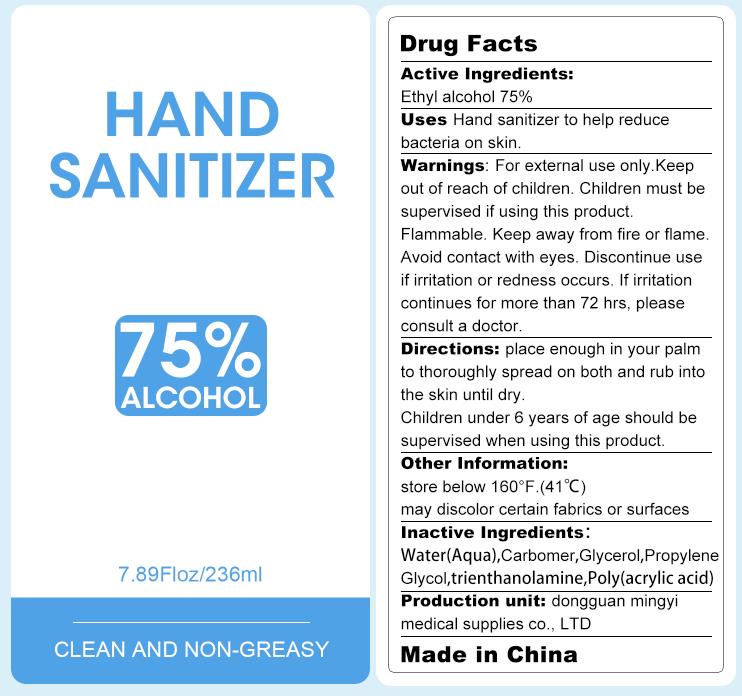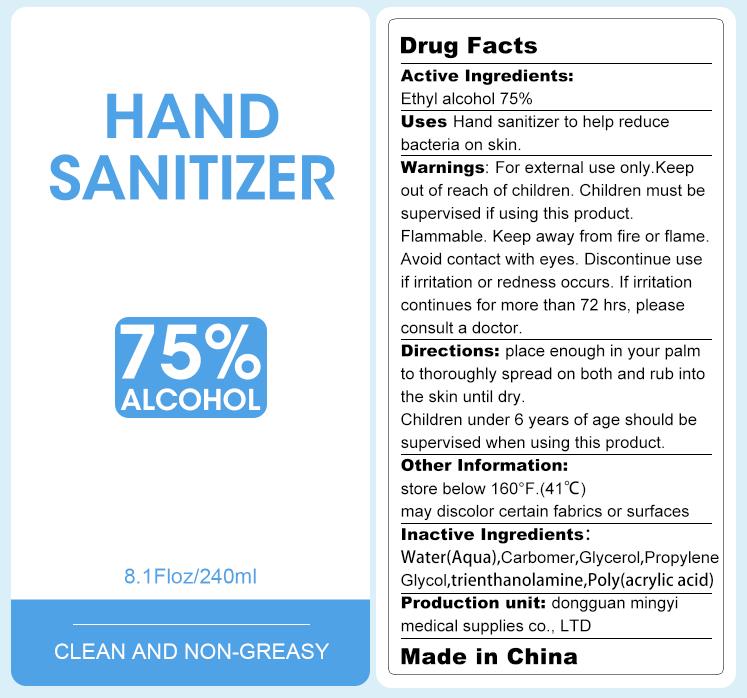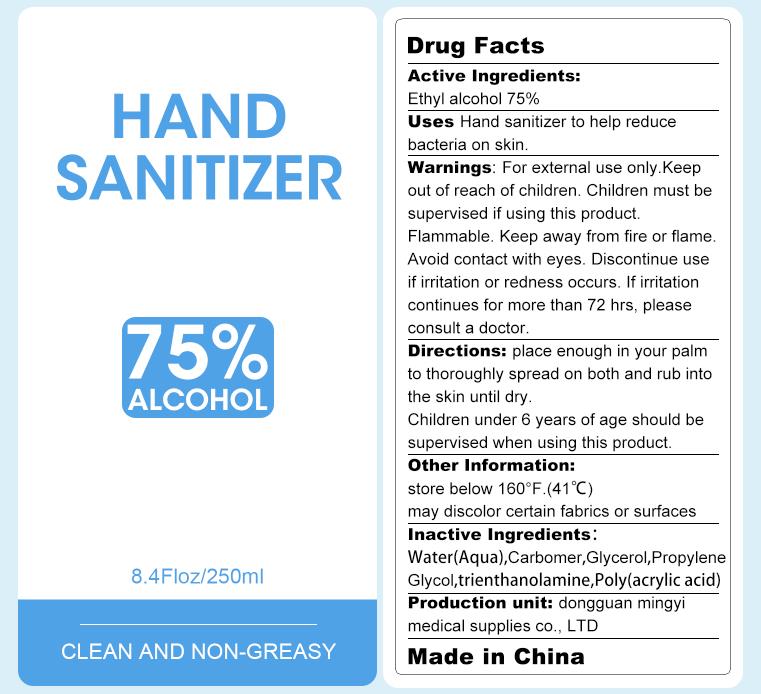 DRUG LABEL: Hand Sanitizer Gel
NDC: 74046-001 | Form: GEL
Manufacturer: Dongguan Mingyi Medical Products  Co., Ltd.
Category: otc | Type: HUMAN OTC DRUG LABEL
Date: 20220123

ACTIVE INGREDIENTS: ALCOHOL 75 mL/100 mL
INACTIVE INGREDIENTS: WATER; TROLAMINE; ACRYLIC ACID; GLYCERIN; CARBOMER HOMOPOLYMER, UNSPECIFIED TYPE; PROPYLENE GLYCOL

74046-001
Hand Sanitizer Gel

Active Ingredients

Ethyl Alcohol 75%

Uses

Hand Sanitizer to help reduce bacteria on skin.

Warnings

For external use only.Keep out of reach of children.Children must be supervised if using this product.

Flammable.Keep away from fire or flame.

Avoid contact with eyes.Discontinue use if irritation or redness occurs.If irritation continues for more than 72hrs, please

consult a doctor.

Directions

Place enough in your palm to thoroughly spread on both and rub into the skin until dry.

Children under 6 years of age should be supervised when using this product.

Other Information

store below 160°F.(41℃)

may discolor certain fabrics or surfaces

Inactive Ingredients

Water(Aqua),Carbomer, Glycerol,Propylene Glycol,triethanolamine,Poly(acrylic acid)